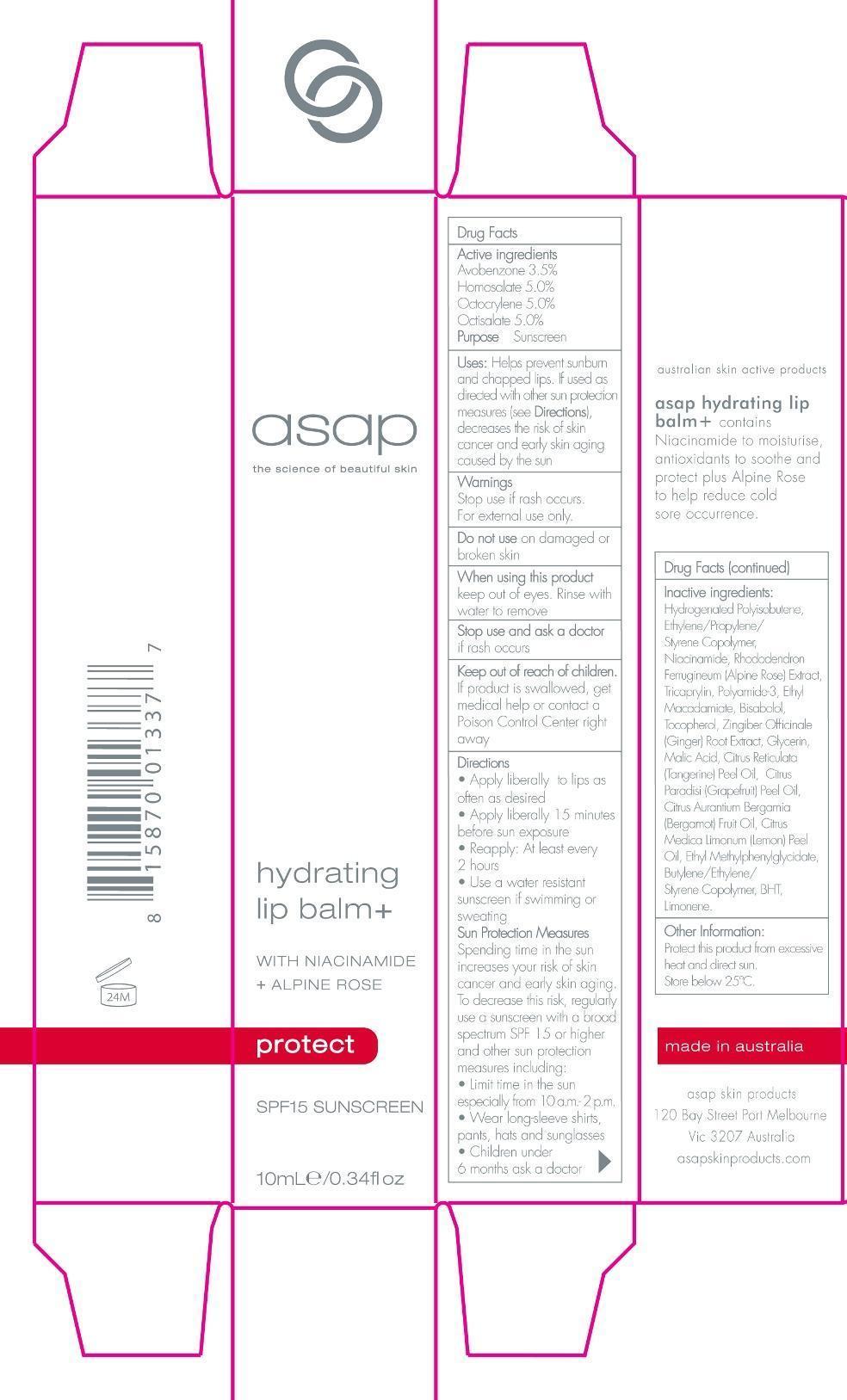 DRUG LABEL: Hydrating Lip Balm SPF 15 sunscreen
NDC: 76261-127 | Form: GEL
Manufacturer: AUSTRALIAN SKIN PRODUCTS PTY LTD
Category: otc | Type: HUMAN OTC DRUG LABEL
Date: 20140807

ACTIVE INGREDIENTS: AVOBENZONE 3.5 g/100 mL; HOMOSALATE 5.0 g/100 mL; OCTOCRYLENE 5.0 g/100 mL; OCTISALATE 5.0 g/100 mL
INACTIVE INGREDIENTS: HYDROGENATED POLYBUTENE (1300 MW); NIACINAMIDE; TRICAPRYLIN; ETHYL MACADAMIATE; .ALPHA.-BISABOLOL, (+)-; TOCOPHEROL; GINGER; MALIC ACID; MANDARIN OIL; GRAPEFRUIT OIL; BERGAMOT OIL; LEMON OIL; ETHYL METHYLPHENYLGLYCIDATE; BUTYLATED HYDROXYTOLUENE; LIMONENE, (+)-

hydrating lip balm SPF 15 Sunscreen

Active Ingredients Purpose

Avobenzone 3.5% Sunscreen

Homosalate 5.0% Sunscreen

Octocrylene 5.0% Sunscreen

Octisalate 5.0% Sunscreen

PURPOSE

Uses: Helps prevent sunburn and chapped lips. If used as directed with other sun protection measures (see Directions), decreases the risk of skin cancer and early skin aging caused by the sun.

Keep out of reach of children. If product is swallowed, get medical help or contact a Poison Control Center right away.

Stop use and ask a doctor if rash occurs.

Warnings:

For external use only

Do not use on damaged or broken skin

When using this product keep out of eyes. Rinse with water to remove

Directions

Apply Liberally to lips as often as desired

Apply liberally 15 minutes before sun exposure

Reapply: at least every 2 hours

Use a water resistant sunscreen if swimming or sweating

Sun Protectection measures. Spending time in the sun increases your risk of skin cancer and early skin aging. To decrease this risk, regularly

use a sunscreen with a broad spectrum SPF 15 or higher and other skin protection measures including:

- Limit time in the sun especially from 10 a.m. -2 p.m.

- Wear long-sleeve shirts, pants, and sunglasses

- Children under 6 months ask a doctor

INACTIVE INGREDIENT

Hydrogenated Polysiobutene, Ethylene/Propylene/Styrene Copolymer, Nicinamide, Rohododendron Ferruineum (Alpine Rose) Extract, Tricaprylin, Polyamide-3, Ethyl Macadamiate, Bisabolol, Tocopherol, Zingiber Officinale (Ginger) Root Extract, Glycerin, Malic Acid, Citrus Reticulata (Tangerine) Peel Oil, Citrus Paradisi (Grapefruit) Peel Oil, Citrus Aurantium Bergamia (Bergamot) Fruit Oil, Citrus Medica Limonium (Lemon) peel Oil, Ethyl Methylphenylglycidate, Butylene/Ethylene/Styrene Copolymer, BHT,limonene.

PACKAGE LABEL

asap

the science of beautiful

hydrating lip balm+

with niacinamide +Alpine Rose
protect

SPF 15 SUNSCREEN

10mL/0.34floz